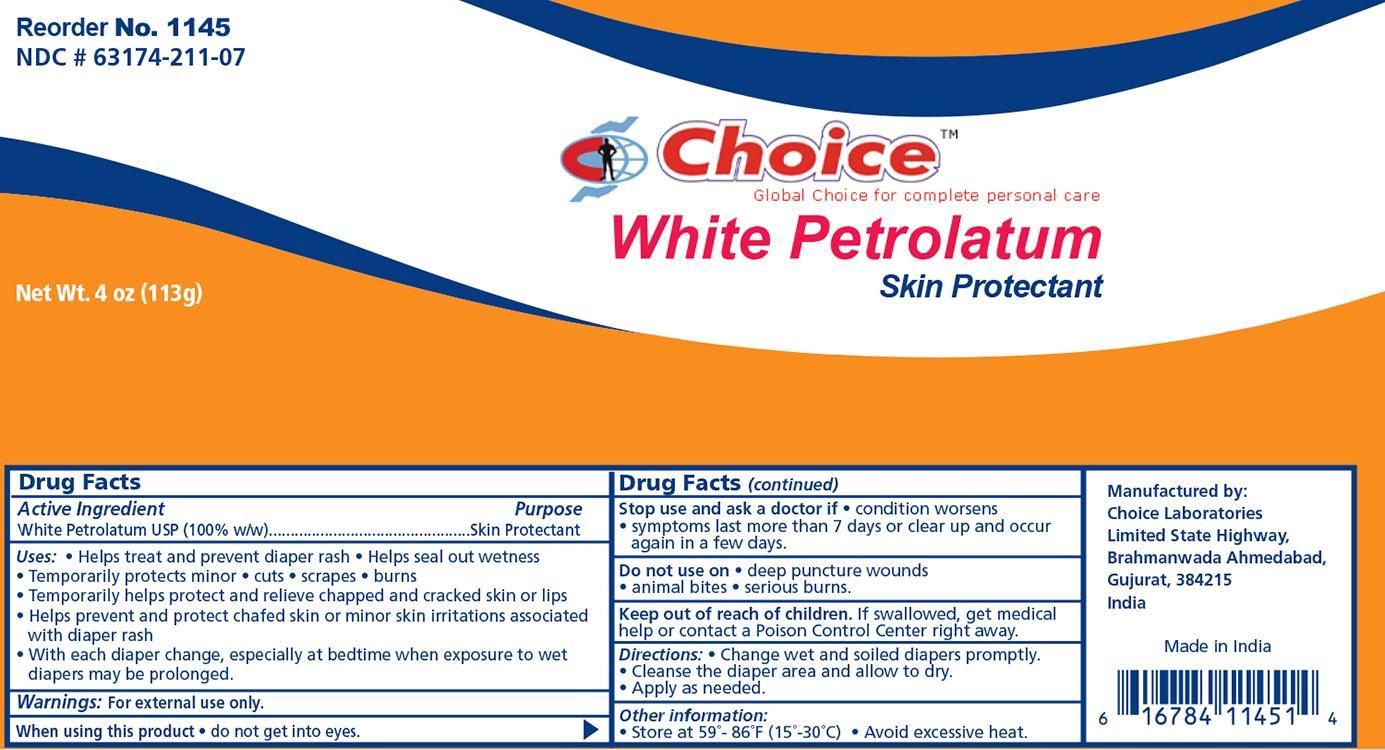 DRUG LABEL: Petrolatum
NDC: 63174-211 | Form: JELLY
Manufacturer: Choice Laboratories Limited
Category: otc | Type: HUMAN OTC DRUG LABEL
Date: 20150518

ACTIVE INGREDIENTS: PETROLATUM 1 g/1 g

Petrolatum Jelly

Active Ingredient Purpose

White Petrolatum 100% Skin Protectant

Uses:

- Helps treat and prevent diaper rash
- Helps seal out wetness
- Temporarily protects minor * cuts * scrapes * burns
- Temporarily helps protect and helps relieve chapped and cracked skin and lips
- Helps prevent and protect from the drying effects of wind and cold weather
- Helps prevent and protect chaffed skin or minor skin irritations associated with diaper rash
- With each diaper change, especially at bed time when exposure to wet diapers may be prolonged.

Warnings:

For external use only.

When using this product:

Do not get in eyes.

Stop use and ask a doctor if:

- Condition worsens
- symptoms last more than 7 days or clear up and occur in a few days.

Do not use on:

- Deep or puncture wounds
- animal bites
- serious burns

Keep out of reach of children

If swallowed, get medical help or contact a Poison Control Center right away

Directions:

- Change wet and soiled diapers promptly
- cleanse the diaper area and allow to dry
- apply as needed

Other information:

- Store at room temperature 15 Deg C - 30 Deg C (59 Deg F - 86 Deg F)
- Avoid excessive heat

Indications and Usage

Skin Protectant

Principal Display Panel

CHPetrolatum.jpg